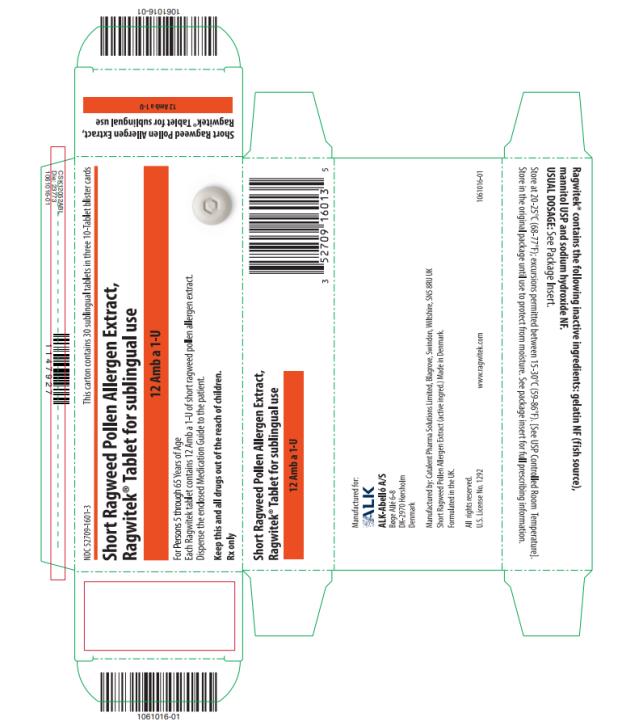 DRUG LABEL: RAGWITEK
NDC: 52709-1601 | Form: TABLET
Manufacturer: ALK-Abello A S
Category: other | Type: STANDARDIZED ALLERGENIC
Date: 20220919

ACTIVE INGREDIENTS: AMBROSIA ARTEMISIIFOLIA POLLEN 12 [Amb'a'1'U]/1 1
INACTIVE INGREDIENTS: MARINE COLLAGEN, SOLUBLE; MANNITOL; SODIUM HYDROXIDE

HIGHLIGHTS OF PRESCRIBING INFORMATION

These highlights do not include all the information needed to use RAGWITEK safely and effectively. See full prescribing information for RAGWITEK.
RAGWITEK® (Short Ragweed Pollen Allergen Extract)
Tablet for Sublingual Use
Initial U.S. Approval: 2014

RECENT MAJOR CHANGES

Indications and Usage (1) 04/2021

WARNING: SEVERE ALLERGIC REACTIONS

See full prescribing information for complete boxed warning.

• RAGWITEK can cause life-threatening allergic reactions such as anaphylaxis and severe laryngopharyngeal restriction. (5.1)

• Do not administer RAGWITEK to patients with severe, unstable or uncontrolled asthma. (4)

• Observe patients in the office for at least 30 minutes following the initial dose. (5.1)

• Prescribe auto-injectable epinephrine, instruct and train patients or parents/guardians on its appropriate use, and instruct patients or parents/guardians to seek immediate medical care upon its use. (5.2)

• RAGWITEK may not be suitable for patients with certain underlying medical conditions that may reduce their ability to survive a serious allergic reaction. (5.2)

• RAGWITEK may not be suitable for patients who may be unresponsive to epinephrine or inhaled bronchodilators, such as those taking beta-blockers. (5.2)

1 INDICATIONS AND USAGE

RAGWITEK is an allergen extract indicated as immunotherapy for the treatment of short ragweed pollen-induced allergic rhinitis, with or without conjunctivitis, confirmed by positive skin test or in vitro testing for pollen-specific IgE antibodies for short ragweed pollen. RAGWITEK is approved for use in persons 5 through 65 years of age. (1)

2 DOSAGE AND ADMINISTRATION

For sublingual use only.

- One tablet daily. (2.1)
- Initiate treatment at least 12 weeks before the expected onset of ragweed pollen season and continue treatment throughout the season. (2.2)
- Place the tablet immediately under the tongue. Allow it to remain there until completely dissolved. Do not swallow for at least 1 minute. (2.2)
- Administer the first dose of RAGWITEK under the supervision of a physician with experience in the diagnosis and treatment of allergic diseases. Observe patients in the office for at least 30 minutes following the initial dose. (2.2)

3 DOSAGE FORMS AND STRENGTHS

- Tablet, 12 Amb a 1-Unit (Amb a 1-U) (3)

4 CONTRAINDICATIONS

- Severe, unstable or uncontrolled asthma. (4)
- History of any severe systemic allergic reaction or any severe local reaction to sublingual allergen immunotherapy. (4)
- A history of eosinophilic esophagitis. (4)
- Hypersensitivity to any of the inactive ingredients contained in this product. (4)

5 WARNINGS AND PRECAUTIONS

- Inform patients or parents/guardians of the signs and symptoms of serious allergic reactions and instruct them to seek immediate medical care and discontinue therapy should any of these occur. (5.1)
- In case of oral inflammation or wounds, stop treatment with RAGWITEK to allow complete healing of the oral cavity. (5.7)

6 ADVERSE REACTIONS

- Adverse reactions reported in ≥5% of adults were: throat irritation, oral pruritus, ear pruritus, oral paresthesia, mouth edema, and tongue pruritus. Adverse reactions reported in ≥5% of children and adolescents 5 through 17 years of age were: throat irritation, oral pruritus, ear pruritus, lip swelling, glossodynia, nausea, oral pain, pharyngeal edema, swollen tongue, abdominal pain upper, stomatitis, and enlarged uvula. (6)

To report SUSPECTED ADVERSE REACTIONS, contact ALK-Abelló Inc., a subsidiary of ALK-Abelló A/S, at 1-855-216-6497 or FDA at 1-800-FDA-1088 or www.fda.gov/medwatch.

FULL PRESCRIBING INFORMATION

WARNING: SEVERE ALLERGIC REACTIONS

● RAGWITEK can cause life-threatening allergic reactions such as anaphylaxis and severe laryngopharyngeal restriction. (5.1)

● Do not administer RAGWITEK to patients with severe, unstable or uncontrolled asthma. (4)

● Observe patients in the office for at least 30 minutes following the initial dose. (5.1)

● Prescribe auto-injectable epinephrine, instruct and train patients or parents/guardians on its appropriate use, and instruct patients or parents/guardians to seek immediate medical care upon its use. (5.2)

● RAGWITEK may not be suitable for patients with certain underlying medical conditions that may reduce their ability to survive a serious allergic reaction. (5.2)

● RAGWITEK may not be suitable for patients who may be unresponsive to epinephrine or inhaled bronchodilators, such as those taking beta-blockers. (5.2)

1 INDICATIONS AND USAGE

RAGWITEK® is an allergen extract indicated as immunotherapy for the treatment of short ragweed pollen-induced allergic rhinitis, with or without conjunctivitis, confirmed by positive skin test or in vitro testing for pollen-specific IgE antibodies for short ragweed pollen. RAGWITEK is approved for use in persons 5 through 65 years of age.

RAGWITEK is not indicated for the immediate relief of allergic symptoms.

2 DOSAGE AND ADMINISTRATION

For sublingual use only.

2.1 Dose

One RAGWITEK tablet daily.

2.2 Administration

Administer the first dose of RAGWITEK in a healthcare setting under the supervision of a physician with experience in the diagnosis and treatment of allergic diseases. After receiving the first dose of RAGWITEK, observe the patient for at least 30 minutes to monitor for signs or symptoms of a severe systemic or a severe local allergic reaction. If the patient tolerates the first dose, the patient may take subsequent doses at home.

Take the tablet from the blister unit after carefully removing the foil with dry hands.

Place the tablet immediately under the tongue. Allow it to remain there until completely dissolved. Do not swallow for at least 1 minute.

Wash hands after handling the tablet.

Do not take the tablet with food or beverage. Food or beverage should not be taken for the following 5 minutes after taking the tablet.

Initiate treatment at least 12 weeks before the expected onset of ragweed pollen season and continue treatment throughout the season. The safety and efficacy of initiating treatment in season have not been established.

Data regarding the safety of restarting treatment after missing a dose of RAGWITEK are limited. In the clinical trials, treatment interruptions for up to seven days were allowed.

Prescribe auto-injectable epinephrine to patients prescribed RAGWITEK and instruct them (or their parents/guardians) in the proper use of auto-injectable epinephrine [see Warnings and Precautions (5.2)].

3 DOSAGE FORMS AND STRENGTHS

RAGWITEK is available as 12 Amb a 1-Unit (Amb a 1-U) tablets that are white to off-white, circular with a debossed double hexagon on one side.

4 CONTRAINDICATIONS

RAGWITEK is contraindicated in patients with:

- Severe, unstable or uncontrolled asthma
- A history of any severe systemic allergic reaction
- A history of any severe local reaction after taking any sublingual allergen immunotherapy
- A history of eosinophilic esophagitis
- Hypersensitivity to any of the inactive ingredients [gelatin, mannitol, and sodium hydroxide] contained in this product [see Description (11)].

5 WARNINGS AND PRECAUTIONS

5.1 Severe Allergic Reactions

RAGWITEK can cause systemic allergic reactions including anaphylaxis which may be life-threatening. In addition, RAGWITEK can cause severe local reactions, including laryngopharyngeal swelling, which can compromise breathing and be life-threatening.

Allergic reactions may require treatment with epinephrine. Prescribe auto-injectable epinephrine to patients receiving RAGWITEK. Instruct patients or parents/guardians to recognize the signs and symptoms of a severe allergic reaction and in the proper use of auto-injectable epinephrine. Instruct patients or parents/guardians to seek immediate medical care and to stop treatment with RAGWITEK upon use of auto-injectable epinephrine [see Patient Counseling Information (17)]. See Prescribing Information for epinephrine for complete information.

RAGWITEK may not be suitable for patients with certain medical conditions that may reduce the ability to survive a serious allergic reaction or that may increase the risk of adverse reactions after epinephrine administration. Examples of these medical conditions include but are not limited to: markedly compromised lung function (either chronic or acute); severe mast cell disorder; or cardiovascular disease including unstable angina, recent myocardial infarction, significant arrhythmia, and uncontrolled hypertension. In addition, RAGWITEK may not be suitable for patients who are taking medications that can potentiate or inhibit the effects of epinephrine (see Prescribing Information for epinephrine for information on drug interactions).

Administer the initial dose of RAGWITEK in a healthcare setting under the supervision of a physician with experience in the diagnosis and treatment of allergic diseases and prepared to manage a life-threatening systemic or local allergic reaction. Observe patients in the office for at least 30 minutes following the initial dose of RAGWITEK.

5.2 Upper Airway Compromise

RAGWITEK can cause local reactions in the mouth or throat that could compromise the upper airway [see Adverse Reactions (6.1)]. Consider discontinuation of RAGWITEK in patients who experience persistent and escalating adverse reactions in the mouth or throat.

5.3 Eosinophilic Esophagitis

Eosinophilic esophagitis has been reported in association with sublingual tablet immunotherapy [see Contraindications (4)]. Discontinue RAGWITEK and consider a diagnosis of eosinophilic esophagitis in patients who experience severe or persistent gastro-esophageal symptoms including dysphagia or chest pain.

5.4 Asthma

Subjects with asthma who participated in clinical trials had asthma of a severity that required, at most, a daily medium dose of an inhaled corticosteroid. RAGWITEK has not been studied in subjects with severe asthma.

Withhold immunotherapy with RAGWITEK if the patient is experiencing an acute asthma exacerbation. Reevaluate patients who have recurrent asthma exacerbations and consider discontinuation of RAGWITEK.

5.5 Concomitant Allergen Immunotherapy

RAGWITEK has not been studied in subjects who are receiving concomitant allergen immunotherapy. Concomitant dosing with other allergen immunotherapy may increase the likelihood of local or systemic adverse reactions to either subcutaneous or sublingual allergen immunotherapy.

5.6 Oral Inflammation

Stop treatment with RAGWITEK to allow complete healing of the oral cavity in patients with oral inflammation (e.g., oral lichen planus, mouth ulcers, or thrush) or oral wounds, such as those following oral surgery or dental extraction.

6 ADVERSE REACTIONS

Adverse reactions reported in ≥5% of adults were: throat irritation, oral pruritus, ear pruritus, oral paresthesia, mouth edema, and tongue pruritus. Adverse reactions reported in ≥5% of children and adolescents 5 through 17 years of age were: throat irritation, oral pruritus, ear pruritus, lip swelling, glossodynia, nausea, oral pain, pharyngeal edema, swollen tongue, abdominal pain upper, stomatitis, and enlarged uvula.

6.1 Clinical Trials Experience

Because clinical trials are conducted under widely varying conditions, adverse reaction rates observed in the clinical trials of a drug cannot be directly compared to rates in the clinical trials of another drug and may not reflect the rates observed in clinical practice.

Adults

In 4 placebo-controlled clinical trials, 1057 subjects 18 years of age and older with short ragweed pollen-induced rhinitis, with or without conjunctivitis, received at least one dose of RAGWITEK, of whom 327 (31%) completed at least 12 weeks of therapy. Of the subjects treated with RAGWITEK, 52% were male, 25% had mild asthma, and 82% were sensitized to other allergens in addition to ragweed pollen. The subject population was 83% White, 12% African American, and 2% Asian. Subject demographics in placebo-treated subjects were similar to the active group. The pooled analysis includes safety data from two 28-day safety studies and safety data from the first 28 days of two 52-week safety and efficacy studies. Adverse reactions reported in ≥1% of subjects in the 28-day pooled analysis treated with RAGWITEK are shown in Table 1.

The most common adverse reactions reported in subjects treated with RAGWITEK were throat irritation (16.6% vs 3.3% placebo), oral pruritus (10.9% vs 2.0%), ear pruritus (10.4% vs 1.1%), and oral paresthesia (10.0% vs 4.0%). The percentage of subjects who discontinued from the clinical trials because of an adverse reaction while exposed to RAGWITEK or placebo was 4.4% and 0.8%, respectively. The most common adverse reactions that led to study discontinuation in subjects who were exposed to RAGWITEK were mouth edema, swollen tongue, and dysphagia.

One subject (1/1057; 0.1%) who received RAGWITEK experienced a treatment-related severe systemic allergic reaction that led to discontinuation of RAGWITEK. The subject had local reactions starting on Day 1 of treatment with RAGWITEK. On Day 6 symptoms progressed and included swelling of the throat, dyspnea, nausea, and lightheadedness. The subject fully recovered after treatment with epinephrine (self-administered), antihistamines, and oral corticosteroids.

Table 1: Adverse Reactions Reported in ≥1% of Adults Treated with RAGWITEK or Placebo (28-day pooled analysis)
Adverse Reaction | RAGWITEK (N=1057) | Placebo (N=757)
Ear and Labyrinth Disorders Ear pruritus | 10.4% | 1.1%
Respiratory, Thoracic and Mediastinal Disorders Throat irritation Oropharyngeal pain Throat tightness | 16.6% 1.5% 1.3% | 3.3% 0.7% 0.5%
Gastrointestinal Disorders Oral pruritus Paresthesia oral Mouth edema Tongue pruritus Lip swelling Swollen tongue Lip pruritus Dry mouth Tongue edema Nausea Palatal edema Dysphagia | 10.9% 10.0% 6.1% 5.1% 3.0% 2.9% 1.5% 1.4% 1.3% 1.1% 1.1% 1.0% | 2.0% 4.0% 0.5% 0.5% 0.4% 0.5% 0.1% 0.7% 0.5% 0.3% 0% 0%
Skin and Subcutaneous Tissue Disorders Pruritus | 1.8% | 1.3%
General Disorders and Administration Site Conditions Chest discomfort | 1.0% | 0%

* 1036 subjects were 18 through 65 years of age and 21 subjects were older than 65 years of age.

† 746 subjects were 18 through 65 years of age and 11 subjects were older than 65 years of age.

The overall safety profile beyond Day 28 in the two 52-week trials was similar to that observed in the pooled 28-day analysis.

Children and Adolescents (5 through 17 years of age)

In 1 placebo-controlled clinical trial, 513 subjects 5 through 17 years of age with short ragweed pollen-induced rhinitis, with or without conjunctivitis, received at least one dose of RAGWITEK. Of the subjects treated with RAGWITEK, 63% were male, 43% had asthma, and 79% were sensitized to other allergens in addition to ragweed pollen. The subject population was 93% White, 3.1% African American, 2.3% multiple race, 1% Asian, 0.5% Native Hawaiian or Other Pacific Islander, and 0.1% American Indian or Alaska Native. Approximately 40% of subjects were children (5 through 11 years of age) and 60% of subjects were adolescents (12 through 17 years of age). Subject demographics in placebo-treated subjects were similar to the active treatment group.

In the trial in children and adolescents 5 through 17 years of age, parents/ guardians and/ or participants were provided SLIT report cards in which they recorded the occurrence of specific solicited adverse reactions daily for the first 28 days following treatment initiation with RAGWITEK or placebo (summarized in Table 2).

Table 2: Solicited* Adverse Reactions occurring within 28 days of Initiation of Treatment with RAGWITEK or Placebo in Children and Adolescents 5 through 17 Years of Age
Adverse Reaction (Any Intensity) | RAGWITEK (N=513) | Placebo (N=509)
Ear and Labyrinth Disorders Itching in the ear | 33.9% | 6.3%
Gastrointestinal Disorders Itching in the mouth Mouth pain Swelling of the lips Nausea Swelling of the tongue† Stomach pain Swelling of the uvula/back of the mouth‡ Mouth ulcer/sore in the mouth Tongue ulcer/sore on the tongue Diarrhea Vomiting | 47.8% 18.9% 13.8% 11.5% 11.3% 10.1% 9.9% 8.4% 6.8% 2.7% 1.2% | 11.2% 4.5% 1.2% 3.3% 0.8% 4.5% 0.4% 2.2% 2.2% 1.2% 0%
Nervous System Disorders Taste alteration/food tastes different | 3.9% | 2.0%
Respiratory, Thoracic and Mediastinal Disorders Throat irritation/tickle Throat swelling | 48.3% 10.7% | 17.7% 1.6%

* Solicited adverse reactions (modified from World Allergy Organization [WAO] list of local side effects of sublingual immunotherapy [SLIT]) were those solicited from subjects via SLIT report card within the first 28 days after treatment initiation.

† Of those subjects reporting any intensity of swelling of the tongue in the RAGWITEK group, 1 subject (0.2%) reported severe intensity of swelling of the tongue. Adverse reactions were categorised as severe according to the definition ‘incapacitating with inability to work or do usual activity’, as assessed by the investigator.

‡ The percentage of subjects reporting "swelling of the uvula/back of the mouth" includes subjects with an enlarged uvula, palatal swelling/edema, and/or mouth swelling/edema (which can be anywhere in the mouth, not specifically at the back of the mouth).

In the clinical trial in children and adolescents, unsolicited adverse reactions occurring throughout the entire duration of the trial were recorded in electronic diaries or reported at study visits. Unsolicited adverse reactions reported by ≥1% of children and adolescents throughout the entire duration of the trial are shown in Table 3.

Table 3: Unsolicited Adverse Reactions occurring during the Entire Trial after Initiation of Treatment, Reported in ≥1% of Children and Adolescents 5 through 17 Years of Age Treated with RAGWITEK or Placebo
Adverse Reaction | RAGWITEK (N=513) | Placebo (N=509)
Ear and Labyrinth Disorders Ear pruritus | 4.5% | 0.2%
Gastrointestinal Disorders Oral pruritus Tongue pruritus Lip swelling Paresthesia oral Mouth swelling Dysphagia Nausea Oral pain Swollen tongue | 7.8% 4.5% 1.9% 1.9% 1.8% 1.6% 1.6% 1.6% 1.4% | 1.0% 0.4% - 0.4% - 0.2% 0.4% 0.4% -
Respiratory, Thoracic and Mediastinal Disorders Throat irritation Oropharyngeal pain Sneezing Pharyngeal edema Rhinorrhea | 7.6% 1.8% 1.6% 1.2% 1.2% | 1.6% 0.4% 0.4% - 0.4%
Skin and Subcutaneous Tissue Disorders Pruritus | 1.2% | 0.2%

The percentage of subjects who discontinued from the clinical trial because of an adverse reaction while exposed to RAGWITEK or placebo was 3.9% and 1.0%, respectively. The most common adverse reaction that led to study discontinuation in subjects who were exposed to RAGWITEK was throat irritation.

Three subjects (0.6%) treated with RAGWITEK and one subject (0.2%) treated with placebo experienced treatment-related systemic allergic reactions [adverse reactions marked with an asterisk (*) were included in Table 3].

- One subject treated with RAGWITEK reported hypersensitivity events (skin/face/neck itching*, eye itching/swelling, sneezing*, runny*/itching nose, neck/abdomen redness) beginning on day 6 (i.e., outside the ragweed pollen season) that resolved by day 26. The events resolved within minutes to less than an hour. On two occasions, the subject was treated with antihistamine. This subject subsequently discontinued the trial on day 34 due to persistent local allergic symptoms (swollen tongue).
- The second subject treated with RAGWITEK reported hypersensitivity (generalized rash on body and face) on day 26 (i.e., outside the ragweed pollen season). The event was treated with antihistamine and systemic corticosteroids and resolved in one week; the subject discontinued the trial due to the event.
- The third subject treated with RAGWITEK reported pruritus* (on cheeks, arms and legs) and dyspnea on day 1 (i.e., outside the ragweed pollen season) after administration of the first dose. Both adverse events resolved within 2 hours without treatment and did not reoccur upon restarting trial medication 1 week later. The subject subsequently completed the trial.
- The subject treated with placebo reported hypersensitivity (papular rash with itching on hands, body and lower limbs) on day 7 (i.e. outside the ragweed pollen season). The event was treated with an antihistamine and systemic corticosteroid and resolved in one week; the subject discontinued the trial due to the event.

One subject (0.2%) treated with RAGWITEK and no subjects on placebo, reported adverse reactions that were treated with epinephrine (any route).The one subject treated with RAGWITEK experienced severe laryngitis on day 126 (during the ragweed pollen season), for which the subject was hospitalized and treated with inhaled racemic epinephrine (i.e., not systemic epinephrine); the laryngitis resolved in 2 days.

6.2 Postmarketing Experience

The following adverse reactions have been identified during post-approval use of RAGWITEK. Because these reactions are reported voluntarily from a population of uncertain size, it is not always possible to reliably estimate their frequency or establish a causal relationship to drug exposure.

- Ear and Labyrinth Disorders: ear discomfort, ear pain
- Gastrointestinal Disorders: gastroesophageal reflux disease, glossodynia, dyspepsia, hypoesthesia oral
- General disorder and administration site conditions: sensation of foreign body
- Immune System Disorders: serious systemic allergic reactions, including anaphylaxis
- Nervous System Disorders: paresthesia
- Respiratory, Thoracic and Mediastinal Disorders: asthma exacerbation, cough, dry throat, dysphonia, pharyngeal erythema
- Skin and Subcutaneous Tissue Disorders: angioedema, urticaria.

8 USE IN SPECIFIC POPULATIONS

8.1 Pregnancy

Risk Summary

All pregnancies have a risk of birth defect, loss, or other adverse outcomes. In the U.S. general population, the estimated background risk of major birth defects and miscarriage in clinically recognized pregnancies is 2% to 4% and 15% to 20%, respectively. Available human data do not establish the presence or absence of RAGWITEK-associated risks during pregnancy.

In an embryo/fetal developmental toxicity study, RAGWITEK subcutaneously administered to mice during gestation at doses up to approximately 3 times the human sublingual dose did not reveal adverse developmental outcomes in fetuses (see 8.1 Data).

Data

Animal Data

In a developmental toxicity study, the effect of RAGWITEK on embryo/fetal development was evaluated in mice. Animals were administered RAGWITEK subcutaneously daily from day 6 to day 15 of the gestation period at doses approximately 1 to 3 times the human sublingual dose of 12 Amb a 1-U. There were no RAGWITEK-related post-implantation losses, fetal malformations or variations.

8.2 Lactation

Risk Summary

It is not known whether RAGWITEK is excreted in human milk. Data are not available to assess the effects of RAGWITEK on the breastfed child or on milk production/excretion. The developmental and health benefits of breastfeeding should be considered along with the mother’s clinical need for RAGWITEK and any potential adverse effects on the breastfed child from RAGWITEK or from the underlying maternal condition.

8.4 Pediatric Use

Efficacy and safety of RAGWITEK have been established in children and adolescents 5 through 17 years of age. The efficacy and safety in pediatric patients below 5 years of age have not been established.

8.5 Geriatric Use

RAGWITEK is not approved for use in patients over 65 years of age because safety and efficacy have not been established.

11 DESCRIPTION

RAGWITEK tablets contain pollen allergen extract from Short Ragweed (Ambrosia artemisiifolia). RAGWITEK is a sublingual tablet that dissolves within 10 seconds.

RAGWITEK is available as a tablet of 12 Amb a 1-U of short ragweed pollen allergen extract.

Inactive ingredients: gelatin NF (fish source), mannitol USP, and sodium hydroxide NF.

12 CLINICAL PHARMACOLOGY

12.1 Mechanism of Action

The precise mechanisms of action of allergen immunotherapy are not known.

13 NONCLINICAL TOXICOLOGY

13.1 Carcinogenesis, Mutagenesis, Impairment of Fertility

No studies have been performed in animals to evaluate the carcinogenic potential of RAGWITEK.

There were no positive findings in a combined in vivo Comet and micronucleus assay in rats using Short Ragweed (Ambrosia artemisiifolia) pollen allergen extract.

Fertility studies have not been performed with Short Ragweed pollen allergen extract.

14 CLINICAL STUDIES

Adults

The efficacy of RAGWITEK in the treatment of ragweed pollen-induced allergic rhinitis, with or without conjunctivitis, was investigated in two double-blind, placebo-controlled clinical trials in adults 18 through 50 years of age. Subjects received RAGWITEK or placebo for approximately 12 weeks prior to the start of the ragweed pollen season and throughout the ragweed pollen season.

The subject population was 86% White, 9% African American, and 3% Asian. The subject population was almost equally divided between males and females. Overall, the mean age of subjects was 36 years. Subjects with asthma who participated in clinical trials had asthma of a severity that required, at most, a daily low dose of an inhaled corticosteroid. Approximately 16% of subjects had mild asthma at baseline.

Efficacy was established by self-reporting of rhinoconjunctivitis daily symptom scores (DSS) and daily medication scores (DMS). Daily rhinoconjunctivitis symptoms included four nasal symptoms (runny nose, stuffy nose, sneezing, and itchy nose), and two ocular symptoms (gritty/itchy eyes and watery eyes). The rhinoconjunctivitis symptoms were measured on a scale of 0 (none) to 3 (severe). Subjects in clinical trials were allowed to take symptom-relieving medications (including systemic and topical antihistamines, and topical and oral corticosteroids) as needed. The daily medication score measured the use of standard open-label allergy medications. Predefined values were assigned to each class of medication. Generally, systemic and topical antihistamines were given the lowest score, topical steroids an intermediate score, and oral corticosteroids the highest score.

The sums of the DSS and DMS were combined into the Total Combined Score (TCS) which was averaged over the peak ragweed pollen season. Also, in each study, the average TCS over the entire ragweed season was assessed. Other endpoints in both studies included the average DSS during the peak and entire ragweed season, and the average DMS during the peak ragweed season.

Trial 1

The first study was a placebo-controlled trial which evaluated subjects 18 through 50 years of age comparing RAGWITEK (n=187) and placebo (n=188) administered as a sublingual tablet daily. In this trial, approximately 22% of subjects had mild asthma and 85% were sensitized to other allergens in addition to short ragweed. Subjects with asthma who participated in this trial had asthma of a severity that required, at most, a daily low dose of an inhaled corticosteroid. Subjects with a clinical history of symptomatic allergies to non-short ragweed pollen allergens that required treatment during the ragweed pollen season were excluded from the trial. The subject population was 78% White, 12% African American, and 8% Asian, and almost equally divided between males and females. The mean age of subjects in this study was 35.4 years. The two treatment groups were balanced with regard to baseline characteristics. The results of this study are shown in Table 4.

Trial 2

The second study was a placebo-controlled trial which evaluated subjects 18 through 50 years of age comparing RAGWITEK (n=194) and placebo (n=198) administered as a sublingual tablet daily. Approximately 17% of subjects had mild asthma and 78% were sensitized to other allergens in addition to short ragweed. Subjects with asthma who participated in this trial had asthma of a severity that required, at most, a daily low dose of an inhaled corticosteroid. Subjects with a clinical history of symptomatic allergies to non-short ragweed pollen allergens that required treatment during the ragweed pollen season were excluded from the trial. The subject population was 88% White, 8.9% African American, 2% Asian, and almost equally divided between males and females. The mean age of subjects in this study was 36.4 years. The two treatment groups were balanced with regard to baseline characteristics. The results of this study are shown in Table 5.

A decrease in TCS during the peak ragweed season for subjects treated with RAGWITEK compared to placebo-treated subjects was demonstrated in both trials. Subjects treated with RAGWITEK also showed a decrease in the average TCS from the start of and throughout the entire ragweed pollen season. Similar decreases were observed in subjects treated with RAGWITEK for other endpoints (see Tables 4 and 5).

Table 4: Adult Trial 1: Total Combined Scores (TCS), Rhinoconjunctivitis Daily Symptom Scores (DSS), and Daily Medication Scores (DMS) During the Ragweed Pollen Season (Adults 18 through 50 Years of Age)
Endpoint* | RAGWITEK (N)† Score‡ | Placebo (N)† Score‡ | Treatment Difference (RAGWITEK – Placebo) | Difference Relative to Placebo§ Estimate (95% CI)
TCS Peak Season¶ | (159) 6.22 | (164) 8.46 | -2.24 | -26% (-38.7, -14.6)
TCS Entire Season | (160) 5.21 | (166) 7.01 | -1.80 | -26% (-37.6, -13.5)
DSS Peak Season | (159) 4.65 | (164) 5.59 | -0.94 | -17% (-28.6, -4.6)
DSS Entire Season | (160) 4.05 | (166) 4.87 | -0.82 | -17% (-28.5, -4.5)
DMS Peak Season | (159) 1.57 | (164) 2.87 | -1.30 | -45% (-65.4, -27.0)

TCS=Total Combined Score (DSS + DMS); DSS=Daily Symptom Score; DMS=Daily Medication Score.

* Parametric analysis using analysis of variance model for all endpoints.

† Number of subjects in analyses.

‡ The estimated group means are reported and difference relative to placebo is based on estimated group means.

§ Difference relative to placebo computed as: (RAGWITEK - placebo)/placebo x 100. The 95% CI was based on the 2.5th and 97.5th percentiles of the 10,000 bootstrap samples.

¶ Peak ragweed season was defined as maximum 15 days with the highest moving average pollen counts during the ragweed season.

Table 5: Adult Trial 2: Total Combined Scores (TCS), Rhinoconjunctivitis Daily Symptom Scores (DSS), and Daily Medication Scores (DMS) During the Ragweed Pollen Season (Adults 18 through 50 Years of Age)
Endpoint* | RAGWITEK (N)† Score‡ | Placebo (N)† Score‡ | Treatment Difference (RAGWITEK – Placebo) | Difference Relative to Placebo§ Estimate (95% CI)
TCS Peak Season¶ | (152) 6.41 | (169) 8.46 | -2.04 | -24% (-36.5, -11.3)
TCS Entire Season | (158) 5.18 | (174) 7.09 | -1.92 | -27% (-38.8, -14.1)
DSS Peak Season | (152) 4.43 | (169) 5.37 | -0.94 | -18% (-29.2, -4.5)
DSS Entire Season | (158) 3.62 | (174) 4.58 | -0.96 | -21% (-31.6, -8.8)
DMS Peak Season | (152) 1.99 | (169) 3.09 | -1.10 | -36% (-55.8, -14.6)

TCS=Total Combined Score (DSS + DMS); DSS=Daily Symptom Score; DMS=Daily Medication Score.

* Parametric analysis using analysis of variance model for all endpoints.

† Number of subjects in analyses.

‡ The estimated group means are reported and difference relative to placebo is based on estimated group means.

§ Difference relative to placebo computed as: (RAGWITEK - placebo)/placebo x 100. The 95% CI was based on the 2.5th and 97.5th percentiles of the 10,000 bootstrap samples.

¶ Peak ragweed season was defined as maximum 15 days with the highest moving average pollen counts during the ragweed season.

Children and Adolescents (5 through 17 years of age)

The efficacy of RAGWITEK in the treatment of ragweed pollen-induced allergic rhinitis, with or without conjunctivitis, was investigated in a double-blind, placebo-controlled clinical trial in children and adolescents 5 through 17 years of age comparing RAGWITEK (n= 512) and placebo (n= 510) administered as a sublingual tablet daily. Subjects received RAGWITEK or placebo 12-20 weeks prior to the start of the ragweed pollen season and throughout the ragweed pollen season. The subject population was 63% male, 93% White, 3.1% African American, 2.3% multiple race, 1% Asian, 0.5% Native Hawaiian or Other Pacific Islander, and 0.1% American Indian or Alaska Native. Approximately 40% of subjects were children (5 through 11 years of age) and 60% of subjects were adolescents (12 through 17 years of age). Subjects with asthma who participated in clinical trials had asthma of a severity that required, at most, a medium dose of an inhaled corticosteroid. 43% of subjects had asthma at baseline. Treatment groups were balanced with regard to baseline characteristics.

Efficacy was established by self-reporting of rhinoconjunctivitis daily symptom scores (DSS) and daily medication scores (DMS) using a similar methodology to the adult trials.

The sums of the DSS and DMS were combined into the Total Combined Score (TCS) which was averaged over the peak ragweed pollen season. The average TCS over the entire ragweed season was also assessed.

A decrease in TCS during the peak ragweed season for subjects treated with RAGWITEK compared to placebo-treated subjects was demonstrated. Subjects treated with RAGWITEK also showed a decrease in the average TCS from the start of and throughout the entire ragweed pollen season. Similar decreases were observed in subjects treated with RAGWITEK for other endpoints (see Table 6).

Table 6: Pediatric Trial: Total Combined Scores (TCS), Rhinoconjunctivitis Daily Symptom Scores (DSS), and Daily Medication Scores (DMS) During the Ragweed Pollen Season for Children and Adolescents 5 through 17 Years of Age
Endpoint* | RAGWITEK (N)† Score‡ | Placebo (N)† Score‡ | Treatment Difference (RAGWITEK – Placebo) | Difference Relative to Placebo§ Estimate (95% CI)
TCS Peak Season¶ | (460) 4.39 | (487) 7.12 | -2.73 | -38% (-46.0, -29.7)
TCS Entire Season | (466) 3.88 | (491) 5.75 | -1.86 | -32% (-40.7, -23.3)
DSS Peak Season | (468) 2.55 | (494) 3.95 | -1.40 | -35% (-43.2, -26.1)
DMS Peak Season | (460) 2.01 | (487) 3.85 | -1.84 | -48% (-59.8, -32.5)

TCS=Total Combined Score (DSS + DMS); DSS=Daily Symptom Score; DMS=Daily Medication Score.

* Parametric analysis using analysis of variance model for all endpoints.

† Number of subjects in analyses.

‡ The estimated group means are reported and difference relative to placebo is based on estimated group means.

§ Difference relative to placebo computed as: (RAGWITEK® - placebo)/placebo x 100. The 95% CI was based on the 2.5th and 97.5th percentiles of the 10,000 bootstrap samples.

¶ Primary endpoint (pre-specified criteria for success for primary endpoint: a treatment difference relative to placebo of at least -15% and the associated upper bound of the 95% confidence interval (CI) for this difference of at least -10%); peak ragweed season was defined as maximum 15 days with the highest moving average pollen counts during the ragweed season.

Note: All statistical analyses for the 4 endpoints included fixed effects of treatment, baseline asthma status (yes, no), age group (5 through 11 years of age, 12 through 17 years of age), pollen season, and pollen region nested within pollen season.

The average DSS during the entire season was 2.27 (RAGWITEK group) and 3.26 (placebo group) (treatment difference of -0.99) with a relative treatment difference of -30% (95% CI -38.6, -20.7) and the average DMS during the entire season was 1.61 (RAGWITEK group) and 2.48 (placebo group) (treatment difference of -0.87) with a relative treatment difference of -35% (95% CI -45.5, -22.7).

16 HOW SUPPLIED/STORAGE AND HANDLING

RAGWITEK 12 Amb a 1-U tablets are white to off-white, circular sublingual tablets with a debossed double hexagon on one side.

RAGWITEK is supplied as follows:

3 blister packages of 10 tablets (30 tablets total). NDC 52709-1601-3

Store at controlled room temperature, 20ºC to 25ºC (68ºF to 77ºF); excursions permitted between 15ºC to 30ºC (59ºF to 86ºF). Store in the original package until use to protect from moisture.

17 PATIENT COUNSELING INFORMATION

Advise patients or parents/guardians to read the FDA-approved patient labeling (Medication Guide) and to keep RAGWITEK and all medicines out of the reach of children.

Severe Allergic Reactions

Advise patients or parents/guardians that RAGWITEK may cause life-threatening systemic or local allergic reactions, including anaphylaxis. Educate patients or parents/guardians about the signs and symptoms of these allergic reactions [see Warnings and Precautions (5.1)]. The signs and symptoms of a severe allergic reaction may include: syncope, dizziness, hypotension, tachycardia, dyspnea, wheezing, bronchospasm, chest discomfort, cough, abdominal pain, vomiting, diarrhea, rash, pruritus, flushing, and urticaria.

Ensure that patients (or their parents/guardians) have auto-injectable epinephrine and instruct patients or parents/guardians in its proper use. Instruct patients (or their parents/guardians) who experience a severe allergic reaction to seek immediate medical care, discontinue RAGWITEK, and resume treatment only when advised by a physician to do so [see Warnings and Precautions (5.1)].

Advise patients or parents/guardians to read the patient information for epinephrine.

Inform patients or parents/guardians that the first dose of RAGWITEK must be administered in a healthcare setting under the supervision of a physician and that they will be monitored for at least 30 minutes to watch for signs and symptoms of life-threatening systemic or local allergic reaction [see Warnings and Precautions (5.1)].

Because of the risk of upper airway compromise, instruct patients (or their parents/guardians) with persistent and escalating adverse reactions in the mouth or throat to discontinue RAGWITEK and to contact their healthcare professional [see Warnings and Precautions (5.2)].

Because of the risk of eosinophilic esophagitis, instruct patients (or their parents/guardians) with severe or persistent symptoms of esophagitis to discontinue RAGWITEK and to contact their healthcare professional [see Warnings and Precautions (5.3)].

Asthma

Instruct patients (or their parents/guardians) with asthma that if they have difficulty breathing or if their asthma becomes difficult to control, they should stop taking RAGWITEK and contact their healthcare professional immediately [see Warnings and Precautions (5.4)].

Administration Instructions

Instruct patients (or their parents/guardians) to carefully remove the foil from the blister unit with dry hands and then take the sublingual tablet immediately by placing it under the tongue where it will dissolve. Also instruct patients (or their parents/guardians) to wash their hands after handling the tablet, and to avoid food or beverages for 5 minutes after taking the tablet [see Dosage and Administration (2.2)].

Manufactured for: ALK-Abelló A/S

ALK-Abelló A/S, Bøge Allé 6-8, DK-2970 Hørsholm, Denmark

U.S. License No. 1292

Manufactured by:

Catalent Pharma Solutions Limited, Blagrove,

Swindon, Wiltshire, SN5 8RU UK

Copyright © 2022 ALK-Abelló A/S.

All rights reserved.

MEDICATION GUIDE

RAGWITEK® (RAG-wi-tek)

(Short Ragweed Pollen Allergen Extract)

Carefully read this Medication Guide before you or your child start taking RAGWITEK® and each time you get a refill. This Medication Guide does not take the place of talking with your doctor about your medical condition or treatment. Talk with your doctor or pharmacist if there is something you do not understand or if you want to learn more about RAGWITEK.

What is the Most Important Information I Should Know about RAGWITEK?

RAGWITEK can cause severe allergic reactions that may be life-threatening. Stop taking RAGWITEK and get medical treatment right away if you or your child have any of the following symptoms after taking RAGWITEK:

- Trouble breathing
- Throat tightness or swelling
- Trouble swallowing or speaking
- Dizziness or fainting
- Rapid or weak heartbeat
- Severe stomach cramps or pain, vomiting, or diarrhea
- Severe flushing or itching of the skin

For home administration of RAGWITEK, your doctor will prescribe auto-injectable epinephrine, a medicine you can inject if you or your child have a severe allergic reaction after taking RAGWITEK. Your doctor will train and instruct you on the proper use of auto-injectable epinephrine.

Talk to your doctor or read the epinephrine patient information if you have any questions about the use of auto-injectable epinephrine.

What is RAGWITEK?

RAGWITEK is a prescription medicine used for sublingual (under the tongue) immunotherapy to treat ragweed pollen allergies that can cause sneezing, runny or itchy nose, stuffy or congested nose, or itchy and watery eyes. RAGWITEK may be prescribed for persons 5 through 65 years of age who are allergic to ragweed pollen.

RAGWITEK is taken for about 12 weeks before ragweed pollen season and throughout ragweed pollen season.

RAGWITEK is NOT a medication that gives immediate relief for symptoms of ragweed allergy.

RAGWITEK is not approved for use in children younger than 5 years of age or in adults older than 65 years of age.

Who Should Not Take RAGWITEK?

You or your child should not take RAGWITEK if:

- You or your child have severe, unstable or uncontrolled asthma
- You or your child had a severe allergic reaction in the past that included any of these symptoms:
  ○ Trouble breathing
  ○ Dizziness or fainting
  ○ Rapid or weak heartbeat
- You or your child have ever had difficulty with breathing due to swelling of the throat or upper airway after using any sublingual immunotherapy before.
- You or your child have ever been diagnosed with eosinophilic esophagitis.
- You or your child are allergic to any of the inactive ingredients contained in RAGWITEK. The inactive ingredients contained in RAGWITEK are: gelatin, mannitol, and sodium hydroxide.

What Should I Tell My Doctor Before Taking RAGWITEK?

Your doctor may decide that RAGWITEK is not the best treatment if:

- You or your child have asthma, depending on how severe it is.
- You or your child suffer from lung disease such as chronic obstructive pulmonary disease (COPD)
- You or your child suffer from heart disease such as coronary artery disease, an irregular heart rhythm, or you have hypertension that is not well controlled.
- You or your daughter are pregnant, plan to become pregnant during the time you will be taking RAGWITEK, or are breast-feeding.
- You or your child are unable or unwilling to administer auto-injectable epinephrine to treat a severe allergic reaction to RAGWITEK.
- You or your child are taking certain medicines that enhance the likelihood of a severe reaction, or interfere with the treatment of a severe reaction. These medicines include:
  ○ beta blockers and alpha-blockers (prescribed for high blood pressure)
  ○ cardiac glycosides (prescribed for heart failure or problems with heart rhythm)
  ○ diuretics (prescribed for heart conditions and high blood pressure)
  ○ ergot alkaloids (prescribed for migraine headache)
  ○ monoamine oxidase inhibitors or tricyclic antidepressants (prescribed for depression)
  ○ thyroid hormone (prescribed for low thyroid activity).
- You or your child are receiving allergy shots or other immunotherapy under the tongue. Use of more than one of these types of medicines together may increase the likelihood of a severe allergic reaction.

You should tell your doctor if you or your child are taking or have recently taken any other medicines, including medicines obtained without a prescription and herbal supplements. Keep a list of them and show it to your doctor and pharmacist each time you get a new supply of RAGWITEK. Ask your doctor or pharmacist for advice before taking RAGWITEK.

Are there any Reasons to Stop Taking RAGWITEK?

Stop RAGWITEK and contact your doctor if you or your child have any of the following after taking RAGWITEK:

- Any type of a serious allergic reaction
- Throat tightness that worsens or swelling of the tongue or throat that causes trouble speaking, breathing, or swallowing
- Asthma or any other breathing condition that gets worse
- Dizziness or fainting
- Rapid or weak heartbeat
- Severe stomach cramps or pain, vomiting, or diarrhea
- Severe flushing or itching of the skin
- Heartburn, difficulty swallowing, pain with swallowing, or chest pain that does not go away or worsens

Also, stop taking RAGWITEK following: mouth surgery procedures (such as tooth removal), or if you develop any mouth infections, ulcers or cuts in the mouth or throat.

How Should I Take RAGWITEK?

Take RAGWITEK exactly as your doctor tells you.

RAGWITEK is a prescription medicine that is placed under the tongue.

- Take the tablet from the blister package after carefully removing the foil with dry hands.
- Place the tablet immediately under the tongue. Allow it to remain there until completely dissolved. Do not swallow for at least 1 minute.
- Do not take RAGWITEK with food or beverage. Food and beverage should not be taken for the following 5 minutes.
- Wash hands after taking the tablet.

Take the first tablet of RAGWITEK in your doctor’s office. After taking the first tablet, you or your child will be watched for at least 30 minutes for symptoms of a serious allergic reaction.

If you tolerate the first dose of RAGWITEK, you or your child will continue RAGWITEK therapy at home by taking one tablet every day. Children should be given each tablet of RAGWITEK by an adult who will watch for any symptoms of a serious allergic reaction.

Take RAGWITEK as prescribed by your doctor until the end of the treatment course. If you forget to take RAGWITEK, do not take a double dose. Take the next dose at your normal scheduled time the next day. If you miss more than one dose of RAGWITEK, contact your healthcare provider before restarting.

What are the Possible Side Effects of RAGWITEK?

In children and adults, the most commonly reported side effects were throat irritation, itching in the mouth or ears, swelling of the lips, mouth or throat, mouth ulcer/sore in the mouth, mouth pain, stomach pain, nausea.

RAGWITEK can cause severe allergic reactions that may be life-threatening. Symptoms of allergic reactions to RAGWITEK include:

- Trouble breathing
- Throat tightness or swelling
- Trouble swallowing or speaking
- Dizziness or fainting
- Rapid or weak heartbeat
- Severe stomach cramps or pain, vomiting, or diarrhea
- Severe flushing or itching of the skin

For additional information on the possible side effects of RAGWITEK talk with your doctor or pharmacist. You may report side effects to the U.S. Food and Drug Administration (FDA) at 1-800-FDA-1088 or www.fda.gov/medwatch.

How Should I Store RAGWITEK?

Keep RAGWITEK out of the reach of children.

Throw away any unused RAGWITEK after the expiration date which is stated on the carton and blister pack after “EXP.”

Store RAGWITEK in a dry place at room temperature, 15ºC to 30ºC (59ºF to 86ºF), in the original package.

General Information about RAGWITEK

Medicines are sometimes prescribed for purposes other than those listed in a Medication Guide. Do not use RAGWITEK for a condition for which it was not prescribed. Do not give RAGWITEK to other people, even if they have the same symptoms. It may harm them.

This Medication Guide summarizes the most important information about RAGWITEK. If you would like more information, talk with your doctor. You can ask your doctor or pharmacist for information about RAGWITEK that was written for healthcare professionals. For more information, go to: www.ragwitek.com or call 1-855-782-9323 (toll-free).

This Medication Guide has been approved by the U.S. Food and Drug Administration.

ALK-Abelló A/S, Bøge Allé 6-8, DK-2970 Hørsholm, Denmark

U.S. License No. 1292

Manufactured by:

Catalent Pharma Solutions Limited, Blagrove,

Swindon, Wiltshire, SN5 8RU UK

Copyright © 2021 ALK-Abelló A/S.

All rights reserved.

Revised: 04/2021

PRINCIPAL DISPLAY PANEL

NDC 52709-1601-3
This carton contains 30 sublingual tablets in three 10-Tablet blister cards

Short Ragweed Pollen Allergen Extract,
Ragwitek® Tablet for sublingual use

12 Amb a 1-U

For Persons 5 through 65 Years of Age
Each Ragwitek tablet contains 12 Amb a 1-U of short ragweed pollen allergen extract.
Dispense the enclosed Medication Guide to the patient.

Keep this and all drugs out of the reach of children.

Rx only